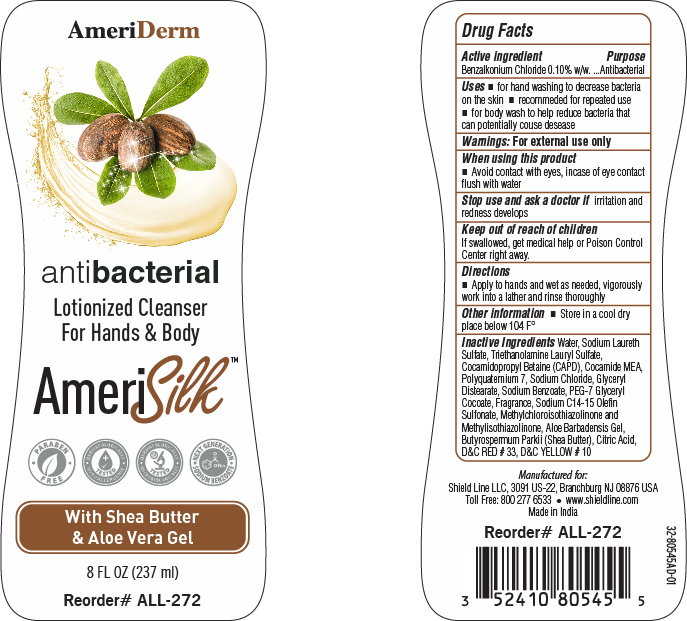 DRUG LABEL: AMERIDERM
NDC: 52410-8054 | Form: SHAMPOO
Manufacturer: SHIELD LINE LLC
Category: otc | Type: HUMAN OTC DRUG LABEL
Date: 20251120

ACTIVE INGREDIENTS: BENZALKONIUM CHLORIDE 0.1 g/100 g
INACTIVE INGREDIENTS: BUTYROSPERMUM PARKII (SHEA) BUTTER; SODIUM BENZOATE; COCAMIDE MEA; METHYLCHLOROISOTHIAZOLINONE; D&C RED NO. 33; SODIUM C14-16 OLEFIN SULFONATE; ALOE VERA LEAF; WATER; COCAMIDOPROPYL BETAINE; CITRIC ACID; EDETATE DISODIUM; SODIUM LAURETH SULFATE; SODIUM CHLORIDE; METHYLISOTHIAZOLINONE; D&C YELLOW NO. 10; POLYQUATERNIUM-7; PEG-7 GLYCERYL COCOATE

AMERIDERM

Active ingredient

Benzalkonium Chloride...0.10% w/w

Purpose

Antibacterial

Uses

• for hand washing to decrease bacteria on the skin • recommended for repeated use
• for body wash to help reduce bacteria that can potentially cause disease

Warnings

For external use only

When using this product

• Avoid contact with eyes, in case of eye contact flush with water

Stop use and ask a doctor

if irritation and redness develops

Keep out of reach of children

If swallowed, get medical help or Poison Control Center right away

Directions

• Apply to hands and wet as needed, vigorously
work into a lather and rinse thoroughly

Other information

Store in a cool dry place below 104 F°

Inactive Ingredients:

Water, Sodium Laureth Sulfate, Triethanolamine Lauryl Sulfate,
Cocamidopropyl Betaine (CAPD), Cocamide MEA,
Polyquaternium 7, Sodium Chloride, Glyceryl Distearate,

Sodium Benzoate, PEG-7 Glyceryl
Cocoate, Fragrance, Sodium C14-15 Olefin Sulfonate,

Methylchloroisothiazolinone and
Methylisothiazolinone, Aloe Barbadensis Gel,
Butyrospermum Parkii (Shea Butter), Citric Acid,
D&C RED # 33, D&C YELLOW # 10